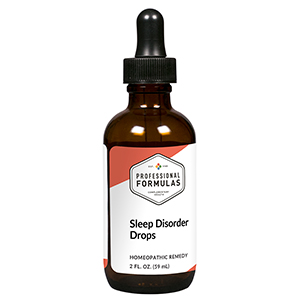 DRUG LABEL: Sleep Disorder Drops
NDC: 63083-2152 | Form: LIQUID
Manufacturer: Professional Complementary Health Formulas
Category: homeopathic | Type: HUMAN OTC DRUG LABEL
Date: 20190815

ACTIVE INGREDIENTS: ARTEMISIA ANNUA FLOWERING TOP 3 [hp_X]/59 mL; ASIAN GINSENG 3 [hp_X]/59 mL; PASSIFLORA INCARNATA FLOWERING TOP 3 [hp_X]/59 mL; SCHISANDRIN B, (+/-)- 3 [hp_X]/59 mL; AMBER 3 [hp_X]/59 mL; RAUWOLFIA SERPENTINA 6 [hp_X]/59 mL; GRAPHITE 8 [hp_X]/59 mL; ACONITUM NAPELLUS WHOLE 9 [hp_X]/59 mL; BARIUM CARBONATE 9 [hp_X]/59 mL; PHOSPHORUS 9 [hp_X]/59 mL; ARNICA MONTANA WHOLE 12 [hp_X]/59 mL; SULFUR 12 [hp_X]/59 mL; ARSENIC TRIOXIDE 30 [hp_X]/59 mL; MERCURIUS SOLUBILIS 30 [hp_X]/59 mL; SEPIA OFFICINALIS JUICE 30 [hp_X]/59 mL
INACTIVE INGREDIENTS: ALCOHOL; WATER

C152

ACTIVE INGREDIENTS

Chamomilla 3X
Panax ginseng 3X
Passiflora incarnata 3X
Schisandra 3X
Succinum 3X
Rauwolfia serpentina 6X
Graphites 8X
Aconitum napellus 9X
Baryta carbonica 9X
Phosphorus 9X
Arnica montana 12X
Sulphur 12X
Arsenicum album 30X
Mercurius solubilis 30X
Sepia 30X

QUESTIONS

Professional Formulas

PO Box 2034 Lake Oswego, OR 97035

INDICATIONS

For the temporary relief of unrestful, interrupted, or inconsistent sleep.*

PURPOSE

*Claims based on traditional homeopathic practice, not accepted medical evidence. Not FDA evaluated.

WARNINGS

In case of overdose, get medical help or contact a poison control center right away.

Keep out of the reach of children.

PREGNANCY OR BREAST FEEDING

If pregnant or breastfeeding, ask a healthcare professional before use.

DIRECTIONS

Place drops under tongue 30 minutes before/after meals. Adults and children 12 years and over: Take 10 drops up to 3 times per day. Consult a physician for use in children under 12 years of age.

OTHER INFORMATION

Tamper resistant. If seal is broken, do not use. After opening, close container tightly and store at room temperature away from heat.

INACTIVE INGREDIENTS

20% ethanol, purified water.

LABEL

Est 1985

Professional Formulas

Complementary Health

Sleep Disorder Drops

Homeopathic Remedy

2 FL. OZ. (59 mL)